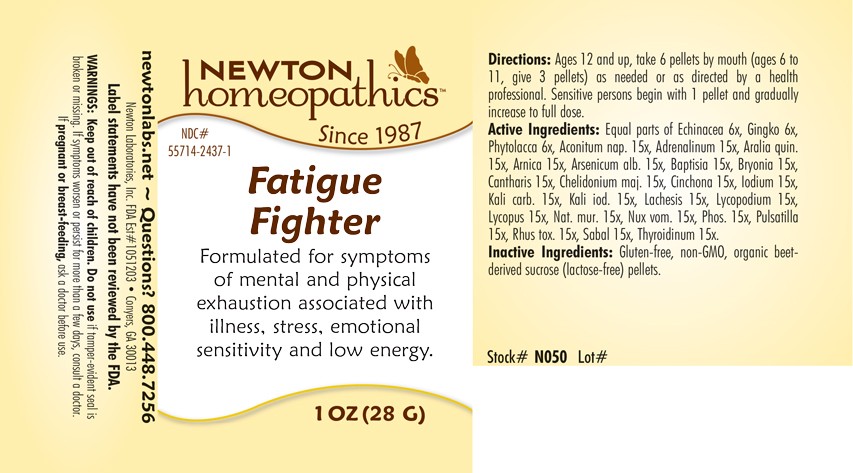 DRUG LABEL: Fatigue Fighter
NDC: 55714-2437 | Form: PELLET
Manufacturer: Newton Laboratories, Inc.
Category: homeopathic | Type: HUMAN OTC DRUG LABEL
Date: 20201125

ACTIVE INGREDIENTS: ACONITUM NAPELLUS 15 [hp_X]/1 g; EPINEPHRINE 15 [hp_X]/1 g; AMERICAN GINSENG 15 [hp_X]/1 g; ARNICA MONTANA 15 [hp_X]/1 g; ARSENIC TRIOXIDE 15 [hp_X]/1 g; BAPTISIA TINCTORIA 15 [hp_X]/1 g; BRYONIA ALBA ROOT 15 [hp_X]/1 g; LYTTA VESICATORIA 15 [hp_X]/1 g; CHELIDONIUM MAJUS 15 [hp_X]/1 g; CINCHONA OFFICINALIS BARK 15 [hp_X]/1 g; IODINE 15 [hp_X]/1 g; POTASSIUM CARBONATE 15 [hp_X]/1 g; POTASSIUM IODIDE 15 [hp_X]/1 g; LACHESIS MUTA VENOM 15 [hp_X]/1 g; LYCOPODIUM CLAVATUM SPORE 15 [hp_X]/1 g; LYCOPUS VIRGINICUS 15 [hp_X]/1 g; SODIUM CHLORIDE 15 [hp_X]/1 g; STRYCHNOS NUX-VOMICA SEED 15 [hp_X]/1 g; PHOSPHORUS 15 [hp_X]/1 g; ANEMONE PULSATILLA 15 [hp_X]/1 g; TOXICODENDRON PUBESCENS LEAF 15 [hp_X]/1 g; SAW PALMETTO 15 [hp_X]/1 g; THYROID, UNSPECIFIED 15 [hp_X]/1 g; ECHINACEA, UNSPECIFIED 6 [hp_X]/1 g; GINKGO 6 [hp_X]/1 g; PHYTOLACCA AMERICANA ROOT 6 [hp_X]/1 g
INACTIVE INGREDIENTS: SUCROSE

Fatigue 2437P

INDICATIONS & USAGE SECTION

Formulated for symptoms of mental and physical exhaustion associated with illness, stress, emotional sensitivity and low energy.

DOSAGE & ADMINISTRATION SECTION

Directions: Ages 12 and up, take 6 pellets by mouth (ages 6 to 11, give 3 pellets) as needed or as directed by a health professional. Sensitive persons begin with 1 pellet and gradually increase to full dose.

OTC - ACTIVE INGREDIENT SECTION

Equal parts of Echinacea 6x,Gingko 6x, Phytolacca 6x, Aconitum nap. 15x, Adrenalinum 15x, Aralia quin.15x, Arnica 15x, Arsenicum alb. 15x, Baptisia 15x, Bryonia 15x, Cantharis 15x, Chelidonium maj.15x, Cinchona 15x, Iodium 15x, Kali carb. 15x, Kali iod. 15x, Lachesis 15x, Lycopodium 15x, Lycopus 15x, Nat. mur. 15x, Nux vom. 15x, Phos.15x, Pulsatilla 15x, Rhus tox.15x, Sabal 15x,Thyroidinum 15x.

OTC - PURPOSE SECTION

Formulated for symptoms of mental and physical exhaustion associated with illness, stress, emotional sensitivity and low energy.

INACTIVE INGREDIENT SECTION

Inactive Ingredients: Gluten-free, non-GMO, organic beet-derived sucrose (lactose-free) pellets.

WARNINGS SECTION

WARNINGS: Keep out of reach of children. Do not use if tamper-evident seal is broken or missing. If symptoms worsen or persist for more than a few days, consult a doctor. If pregnant or breast-feeding, ask a doctor before use.

QUESTIONS SECTION

newtonlabs.net - Questions? 800.448.7256

Newton Laboratories, Inc. FDA Est # 1051203 Conyers, GA 30013

OTC - PREGNANCY OR BREAST FEEDING SECTION

If pregnant or breast-feeding, ask a doctor before use.

OTC - KEEP OUT OF REACH OF CHILDREN SECTION

Keep out of reach of children.